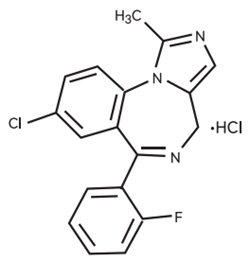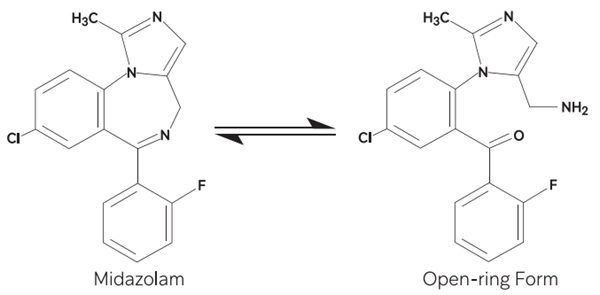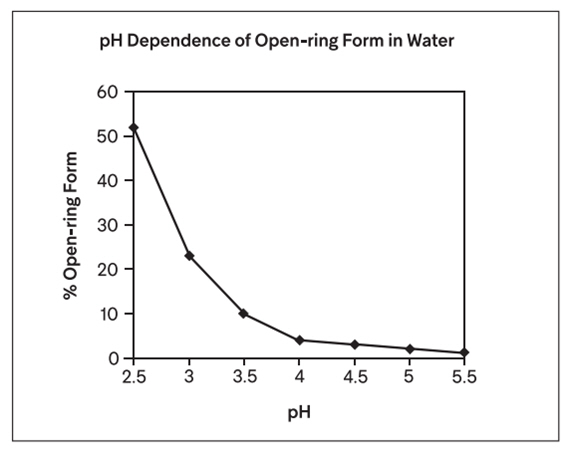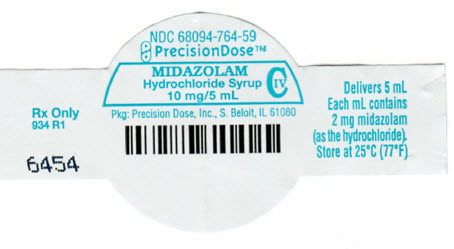 DRUG LABEL: Midazolam Hydrochloride
NDC: 68094-764 | Form: SYRUP
Manufacturer: Precision Dose Inc.
Category: prescription | Type: HUMAN PRESCRIPTION DRUG LABEL
Date: 20250815
DEA Schedule: CIV

ACTIVE INGREDIENTS: Midazolam Hydrochloride 2 mg/1 mL
INACTIVE INGREDIENTS: Anhydrous citric acid; D&C Red No. 33; Edetate disodium; Glycerin; Hydrochloric acid; sodium benzoate; sodium citrate, unspecified form; saccharin sodium; sorbitol; water

MIDAZOLAM HYDROCHLORIDE SYRUP CIV

For oral use

WARNINGS

Personnel and Equipment for Monitoring and Depression

Midazolam HCl syrup has been associated with respiratory depression and respiratory arrest, especially when used for sedation in noncritical care settings. Midazolam HCl syrup has been associated with reports of respiratory depression, airway obstruction, desaturation, hypoxia, and apnea, most often when used concomitantly with other central nervous system depressants. Midazolam HCl Syrup should be used only in hospital or ambulatory care settings, including physicians' and dentists' offices, that can provide for continuous monitoring of respiratory and cardiac function. Immediate availability of resuscitative drugs and age- and size-appropriate equipment for ventilation and intubation, and personnel trained in their use and skilled in airway management should be assured [see WARNINGS]. For deeply sedated patients, a dedicated individual, other than the practitioner performing the procedure, should monitor the patient throughout the procedure.

Risks From Concomitant Use With Opioids

Concomitant use of benzodiazepines and opioids may result in profound sedation, respiratory depression, coma, and death. Monitor patients for respiratory depression and sedation [see WARNINGS, PRECAUTIONS/Drug Interactions].

DESCRIPTION

Midazolam is a benzodiazepine available as midazolam HCl syrup for oral administration. Midazolam, a white to light yellow crystalline compound, is insoluble in water, but can be solubilized in aqueous solutions by formation of the hydrochloride salt in situ under acidic conditions. Chemically, midazolam HCl is 8-chloro-6-(2-fluorophenyl)-1-methyl-4H-imidazo[1,5-a][1,4] benzodiazepine hydrochloride.

Midazolam hydrochloride has the molecular formula C18H13ClFN3∙HCl, a calculated molecular weight of 362.25 and the following structural formula:

Each mL of the syrup contains midazolam hydrochloride equivalent to 2 mg midazolam compounded with bitterness modifier, artificial cherry-brandy flavor, citric acid anhydrous, D&C Red #33, edetate disodium, glycerin, sodium benzoate, sodium citrate, sodium saccharin, sorbitol solution, and water; the pH is adjusted to 2.8 to 3.6 with hydrochloric acid.

Under the acidic conditions required to solubilize midazolam in the syrup, midazolam is present as an equilibrium mixture (shown below) of the closed ring form shown above and an open-ring structure formed by the acid-catalyzed ring opening of the 4,5-double bond of the diazepine ring. The amount of open-ring form is dependent upon the pH of the solution. At the specified pH of the syrup, the solution may contain up to about 40% of the open-ring compound. At the physiologic conditions under which the product is absorbed (pH of 5 to 8) into the systemic circulation, any open-ring form present reverts to the physiologically active, lipophilic, closed-ring form (midazolam) and is absorbed as such.

The following chart below plots the percentage of midazolam present as the open-ring form as a function of pH in aqueous solutions. As indicated in the graph, the amount of open-ring compound present in solution is sensitive to changes in pH over the pH range specified for the product: 2.8 to 3.6. Above pH 5, at least 99% of the mixture is present in the closed-ring form.

CLINICAL PHARMACOLOGY

Midazolam is a short-acting benzodiazepine central nervous system (CNS) depressant.

Pharmacodynamics

Pharmacodynamic properties of midazolam and its metabolites, which are similar to those of other benzodiazepines, include sedative, anxiolytic, amnesic and hypnotic activities. Benzodiazepine pharmacologic effects appear to result from reversible interactions with the γ-amino butyric acid (GABA) benzodiazepine receptor in the CNS, the major inhibitory neurotransmitter in the central nervous system. The action of midazolam is readily reversed by the benzodiazepine receptor antagonist, flumazenil.

Data from published reports of studies in pediatric patients clearly demonstrate that oral midazolam provides safe and effective sedation and anxiolysis prior to surgical procedures that require anesthesia as well as before other procedures that require sedation but may not require anesthesia. The most commonly reported effective doses range from 0.25 to 1.0 mg/kg in children (6 months to <16 years). The single most commonly reported effective dose is 0.5 mg/kg. Time to onset of effect is most frequently reported as 10 to 20 minutes.

The effects of midazolam on the CNS are dependent on the dose administered, the route of administration, and the presence or absence of other medications.

Following premedication with oral midazolam, time to recovery has been assessed in pediatric patients using various measures, such as time to eye opening, time to extubation, time in the recovery room, and time to discharge from the hospital. Most placebo-controlled trials (8 total) have shown little effect of oral midazolam on recovery time from general anesthesia; however, a number of other placebo-controlled studies (5 total) have demonstrated some prolongation in recovery time following premedication with oral midazolam. Prolonged recovery may be related to duration of the surgical procedure and/or use of other medications with central nervous system depressant properties.

Partial or complete impairment of recall following oral midazolam has been demonstrated in several studies. Amnesia for the surgical experience was greater after oral midazolam when used as a premedicant than after placebo and was generally considered a benefit. In one study, 69% of midazolam patients did not remember mask application versus 6% of placebo patients.

Episodes of oxygen desaturation, respiratory depression, apnea, and airway obstruction have been reported in <1% of pediatric patients following premedication (eg, sedation prior to induction of anesthesia) with midazolam HCl syrup; the potential for such adverse events are markedly increased when oral midazolam is combined with other central nervous system depressing agents and in patients with abnormal airway anatomy, patients with cyanotic congenital heart disease, or patients with sepsis or severe pulmonary disease [see WARNINGS].

Concomitant use of barbiturates or other central nervous system depressants may increase the risk of hypoventilation, airway obstruction, desaturation or apnea, and may contribute to profound and/or prolonged drug effect. In one study of pediatric patients undergoing elective repair of congenital cardiac defects, premedication regimens (oral dose of 0.75 mg/kg midazolam or IM morphine plus scopolamine) increased transcutaneous carbon dioxide (PtcCO2), decreased SpO2 (as measured by pulse oximetry), and decreased respiratory rates preferentially in patients with pulmonary hypertension. This suggests that hypercarbia or hypoxia following premedication might pose a risk to children with congenital heart disease and pulmonary hypertension. In a study of an adult population 65 years and older, the preinduction administration of oral midazolam 7.5 mg resulted in a 60% incidence of hypoxemia (paO2<90% for over 30 seconds) at some time during the operative procedure versus 15% for the nonpremedicated group.

Pharmacokinetics

Absorption

Midazolam is rapidly absorbed after oral administration and is subject to substantial intestinal and hepatic first-pass metabolism. The pharmacokinetics of midazolam and its major metabolite, α-hydroxymidazolam, and the absolute bioavailability of midazolam HCl syrup were studied in pediatric patients of different ages (6 months to <16 years old) over a 0.25 to 1.0 mg/kg dose range. Pharmacokinetic parameters from this study are presented in Table 1. The mean Tmax values across dose groups (0.25, 0.5, and 1.0 mg/kg) range from 0.17 to 2.65 hours. Midazolam exhibits linear pharmacokinetics between oral doses of 0.25 to 1.0 mg/kg (up to a maximum dose of 40 mg) across the age groups ranging from 6 months to <16 years. Linearity was also demonstrated across the doses within the age group of 2 years to <12 years having 18 patients at each of the three doses. The absolute bioavailability of the midazolam HCl syrup in pediatric patients is about 36%, which is not affected by pediatric age or weight. The AUC0-∞ ratio of α-hydroxymidazolam to midazolam for the oral dose in pediatric patients is higher than for an IV dose (0.38 to 0.75 versus 0.21 to 0.39 across the age group of 6 months to <16 years), and the AUC0-∞ ratio of α-hydroxymidazolam to midazolam for the oral dose is higher in pediatric patients than in adults (0.38 to 0.75 versus 0.40 to 0.56).

Food effect has not been tested using midazolam HCl syrup. When a 15 mg oral tablet of midazolam was administered with food to adults, the absorption and disposition of midazolam was not affected. Feeding is generally contraindicated prior to sedation of pediatric patients for procedures.

Table 1: Pharmacokinetics of Midazolam Following Single Dose Administration of Midazolam Hydrochloride Syrup
Number of subjects/age group | Dose (mg/kg) | Tmax (h) | Cmax (ng/mL) | t1/2 (h) | AUC0-∞ (ng∙h/mL)
6 months to <2 years old
1 | 0.25 | 0.17 | 28.0 | 5.82 | 67.6
1 | 0.50 | 0.35 | 66.0 | 2.22 | 152
1 | 1.00 | 0.17 | 61.2 | 2.97 | 224
2 to <12 years old
18 | 0.25 | 0.72 ± 0.44 | 63.0 ± 30.0 | 3.16 ± 1.50 | 138 ± 89.5
18 | 0.50 | 0.95 ± 0.53 | 126 ± 75.8 | 2.71 ± 1.09 | 306 ± 196
18 | 1.00 | 0.88 ± 0.99 | 201 ± 101 | 2.37 ± 0.96 | 743 ± 642
12 to <16 years old
4 | 0.25 | 2.09 ± 1.35 | 29.1 ± 8.2 | 6.83 ± 3.84 | 155 ± 84.6
4 | 0.50 | 2.65 ± 1.58 | 118 ± 81.2 | 4.35 ± 3.31 | 821 ± 568
2 | 1.00 | 0.55 ± 0.28 | 191 ± 47.4 | 2.51 ± 0.18 | 566 ± 15.7

Distribution

The extent of plasma protein binding of midazolam is moderately high and concentration independent. In adults and pediatric patients older than 1 year, midazolam is approximately 97% bound to plasma protein, principally albumin. In healthy volunteers, α-hydroxymidazolam is bound to the extent of 89%. In pediatric patients (6 months to <16 years) receiving 0.15 mg/kg IV midazolam, the mean steady-state volume of distribution ranged from 1.24 to 2.02 L/kg.

Metabolism

Midazolam is primarily metabolized in the liver and gut by human cytochrome P450 IIIA4 (CYP3A4) to its pharmacologic active metabolite, α-hydroxymidazolam, followed by glucuronidation of the α-hydroxyl metabolite which is present in unconjugated and conjugated forms in human plasma. The α-hydroxymidazolam glucuronide is then excreted in urine. In a study in which adult volunteers were administered intravenous midazolam (0.1 mg/kg) and α-hydroxymidazolam (0.15 mg/kg), the pharmacodynamic parameter values of the maximum effect (Emax) and concentration eliciting half-maximal effect (EC50) were similar for both compounds. The effects studied were reaction time and errors in tracing tests. The results indicate that α-hydroxymidazolam is equipotent and equally effective as unchanged midazolam on a total plasma concentration basis. After oral or intravenous administration, 63% to 80% of midazolam is recovered in urine as α-hydroxymidazolam glucuronide. No significant amount of parent drug or metabolites is extractable from urine before beta-glucuronidase and sulfatase deconjugation, indicating that the urinary metabolites are excreted mainly as conjugates.

Midazolam is also metabolized to two other minor metabolites: 4-hydroxy metabolite (about 3% of the dose) and 1,4-dihydroxy metabolite (about 1% of the dose) are excreted in small amounts in the urine as conjugates.

Elimination

The mean elimination half-life of midazolam ranged from 2.2 to 6.8 hours following single oral doses of 0.25, 0.5, and 1.0 mg/kg of midazolam HCl syrup. Similar results (ranged from 2.9 to 4.5 hours) for the mean elimination half-life were observed following IV administration of 0.15 mg/kg of midazolam to pediatric patients (6 months to <16 years old). In the same group of patients receiving the 0.15 mg/kg IV dose, the mean total clearance ranged from 9.3 to 11.0 mL/min/kg.

Pharmacokinetic-Pharmacodynamic Relationships

The relationship between plasma concentration and sedation and anxiolysis scores of midazolam HCl syrup (single oral doses of 0.25, 0.5, or 1.0 mg/kg) was investigated in three age groups of pediatric patients (6 months to <2 years, 2 to <12 years, and 12 to <16 years old). In this study, the patient's sedation scores were recorded at baseline and at 10-minute intervals up to 30 minutes after oral dosing until satisfactory sedation ("drowsy" or "asleep but responsive to mild shaking" or "asleep and not responsive to mild shaking") was achieved. Anxiolysis scores were measured at the time when the patient was separated from his/her parents and at mask induction. The results of the analyses showed that the mean midazolam plasma concentration as well as the mean of midazolam plus α-hydroxymidazolam for those patients with a sedation score of 4 (asleep but responsive to mild shaking) is significantly different than the mean concentrations for those patients with a sedation score of 3 (drowsy), which is significantly different than the mean concentrations for patients with a sedation score of 2 (awake/calm). The statistical analysis indicates that the greater the midazolam, or midazolam plus α-hydroxymidazolam concentration, the greater the maximum sedation score for pediatric patients. No such trend was observed between anxiolysis scores and the mean midazolam concentration or mean of midazolam plus α-hydroxymidazolam concentration, however, anxiolysis is a more variable surrogate measurement of clinical response.

Special Populations

Renal Impairment

Although the pharmacokinetics of intravenous midazolam in adult patients with chronic renal failure differed from those of subjects with normal renal function, there were no alterations in the distribution, elimination, or clearance of unbound drug in the renal failure patients. However, the effects of renal impairment on the active metabolite α-hydroxymidazolam are unknown.

Hepatic Dysfunction

Chronic hepatic disease alters the pharmacokinetics of midazolam. Following oral administration of 15 mg of midazolam HCl syrup, Cmax and bioavailability values were 43% and 100% higher, respectively, in adult patients with hepatic cirrhosis than adult subjects with normal liver function. In the same patients with hepatic cirrhosis, following IV administration of 7.5 mg of midazolam, the clearance of midazolam was reduced by about 40% and the elimination half-life was increased by about 90% compared with subjects with normal liver function. Midazolam should be titrated for the desired effect in patients with chronic hepatic disease.

Congestive Heart Failure

Following oral administration of 7.5 mg of midazolam HCl syrup, elimination half-life values were 43% higher in adult patients with congestive heart failure than in control subjects.

Neonates

Midazolam HCl syrup has not been studied in pediatric patients less than 6 months of age.

Drug-Drug Interactions

See PRECAUTIONS: Drug Interactions.

Inhibitors of CYP3A4 Isozymes

Table 2 summarizes the changes in the Cmax and AUC of midazolam when drugs known to inhibit CYP3A4 were concurrently administered with oral midazolam HCl syrup in adult subjects.

Table 2
Interacting Drug | Adult Doses Studied | % Increase in Cmax of Oral Midazolam | % Increase in AUC of Oral Midazolam
Cimetidine | 800 to 1,200 mg up to 4 times a day in divided doses | 6 to 138 | 10 to 102
Diltiazem | 60 mg three times a day | 105 | 275
Erythromycin | 500 mg three times a day | 170 to 171 | 281 to 341
Fluconazole | 200 mg daily | 150 | 250
Grapefruit Juice | 200 mL | 56 | 52
Itraconazole | 100 to 200 mg daily | 80 to 240 | 240 to 980
Ketoconazole | 400 mg daily | 309 | 1,490
Ranitidine | 150 mg two or three times a day; 300 mg daily | 15 to 67 | 9 to 66
Roxithromycin | 300 mg daily | 37 | 47
Saquinavir | 1,200 mg three times a day | 235 | 514
Verapamil | 80 mg three times a day | 97 | 192

Other drugs known to inhibit the effects of CYP3A4, such as protease inhibitors, would be expected to have similar effects on these midazolam pharmacokinetic parameters.

Inducers of CYP3A4 Isozymes

Table 3 summarizes the changes in the Cmax and AUC of midazolam when drugs known to induce CYP3A4 were concurrently administered with midazolam HCl syrup in adult subjects. The clinical significance of these changes is unclear.

Table 3
Interacting Drug | Adult Doses Studied | % Decrease in Cmax of Oral Midazolam | % Decrease in AUC of Oral Midazolam
Carbamazepine | Therapeutic Doses | 93 | 94
Phenytoin | Therapeutic Doses | 93 | 94
Rifampin | 600 mg/day | 94 | 96

Although not tested, phenobarbital, rifabutin and other drugs known to induce the effects of CYP3A4 would be expected to have similar effects on these midazolam pharmacokinetic parameters.

Drugs that did not affect midazolam pharmacokinetics are presented in Table 4.

Table 4
Interacting Drug | Adult Doses Studied
Azithromycin | 500 mg/day
Nitrendipine | 20 mg
Terbinafine | 200 mg/day

Clinical Trials

Dose Ranging, Safety and Efficacy Study with Midazolam Hydrochloride Syrup in Pediatric Patients

The effectiveness of midazolam HCl syrup as a premedicant to sedate and calm pediatric patients prior to induction of general anesthesia was compared among three different doses in a randomized, double-blind, parallel-group study. Patients of ASA physical status I, II or III were stratified to 1 of 3 age groups (6 months to <2 years, 2 to <6 years, and 6 to <16 years), and within each age group randomized to 1 of 3 dosing groups (0.25, 0.5, and 1.0 mg/kg up to a maximum dose of 20 mg). Greater than 90% of treated patients achieved satisfactory sedation and anxiolysis at least one timepoint within 30 minutes posttreatment. Similarly high proportions of patients exhibited satisfactory ease of separation from parent or guardian and were cooperative at the time of mask induction with nitrous oxide and halothane administration. Onset time of satisfactory sedation or anxiolysis occurred within 10 minutes after treatment for >70% of patients who started with an unsatisfactory baseline rating. Whereas pairwise comparisons (0.25 mg/kg versus 0.5 mg/kg groups, and 0.5 mg/kg versus 1.0 mg/kg groups) on satisfactory sedation did not yield significant p-values (p=0.08 in both cases), comparative analysis of the clinical response between the high and low doses demonstrated that a higher proportion of patients in the 1.0 mg/kg dose group exhibited satisfactory sedation and anxiolysis as compared to the 0.25 mg/kg group (p<0.05).

INDICATIONS AND USAGE

Midazolam HCl syrup is indicated for use in pediatric patients for sedation, anxiolysis and amnesia prior to diagnostic, therapeutic or endoscopic procedures or before induction of anesthesia.

Midazolam HCl syrup is intended for use in monitored settings only and not for chronic or home use [see WARNINGS].

CONTRAINDICATIONS

Midazolam HCl syrup is contraindicated in patients with a known hypersensitivity to the drug or allergies to cherries or formulation excipients. Benzodiazepines are contraindicated in patients with acute narrow-angle glaucoma. Benzodiazepines may be used in patients with open-angle glaucoma only if they are receiving appropriate therapy. Measurements of intraocular pressure in patients without eye disease show a moderate lowering following induction of general anesthesia with injectable midazolam; patients with glaucoma have not been studied.

WARNINGS

Personnel and Equipment for Monitoring and Resuscitation

Midazolam HCl syrup should be used only in hospital or ambulatory care settings, including physicians' and dentists' offices, that are equipped to provide continuous monitoring of respiratory and cardiac function. Midazolam HCl syrup must only be administered to patients if they will be monitored by direct visual observation by a health care professional. If midazolam HCl syrup will be administered in combination with other anesthetic drugs or drugs which depress the central nervous system, patients must be monitored by persons specifically trained in the use of these drugs and, in particular, in the management of respiratory effects of these drugs, including respiratory and cardiac resuscitation of patients in the age group being treated.

For deeply sedated patients, a dedicated individual whose sole responsibility is to observe the patient, other than the practitioner performing the procedure, should monitor the patient throughout the procedure.

Patients should be continuously monitored for early signs of hypoventilation, airway obstruction, or apnea with means for detection readily available (eg, pulse oximetry). Hypoventilation, airway obstruction, and apnea can lead to hypoxia and/or cardiac arrest unless effective countermeasures are taken immediately. The immediate availability of specific reversal agents (flumazenil) is highly recommended. Vital signs should continue to be monitored during the recovery period. Because midazolam can depress respiration [see CLINICAL PHARMACOLOGY], especially when used concomitantly with opioid agonists and other sedatives [see DOSAGE AND ADMINISTRATION], it should be used for sedation/anxiolysis/amnesia only in the presence of personnel skilled in early detection of hypoventilation, maintaining a patent airway, and supporting ventilation.

Episodes of oxygen desaturation, respiratory depression, apnea, and airway obstruction have been occasionally reported following premedication (sedation prior to induction of anesthesia) with oral midazolam; such events are markedly increased when oral midazolam is combined with other central nervous system depressing agents and in patients with abnormal airway anatomy, patients with cyanotic congenital heart disease, or patients with sepsis or severe pulmonary disease.

Risks from Concomitant Use with Opioids

Concomitant use of benzodiazepines, including midazolam, and opioids may result in profound sedation, respiratory depression, coma and death. If a decision is made to use midazolam concomitantly with opioids, monitor patients for respiratory depression and sedation [see PRECAUTIONS/Drug Interactions].

Risk of Respiratory Adverse Events

Serious respiratory adverse events have occurred after administration of oral midazolam, most often when midazolam was used in combination with other central nervous system depressants. These adverse events have included respiratory depression, airway obstruction, oxygen desaturation, apnea, and rarely, respiratory and/or cardiac arrest [see BOX WARNING]. When oral midazolam is administered as the sole agent at recommended doses respiratory depression, airway obstruction, oxygen desaturation, and apnea occur infrequently [see DOSAGE AND ADMINISTRATION].

Prior to the administration of midazolam in any dose, the immediate availability of oxygen, resuscitative drugs, age- and size-appropriate equipment for bag/valve/mask ventilation and intubation, and skilled personnel for the maintenance of a patent airway and support of ventilation should be ensured.

Individualization of Dosage

Midazolam HCl syrup must never be used without individualization of dosage, particularly when used with other medications capable of producing central nervous system depression. See DOSAGE AND ADMINISTRATION for complete information.

Other Adverse Events

Reactions such as agitation, involuntary movements (including tonic/clonic movements and muscle tremor), hyperactivity and combativeness have been reported in both adult and pediatric patients. Consideration should be given to the possibility of paradoxical reaction. Should such reactions occur, the response to each dose of midazolam and all other drugs, including local anesthetics, should be evaluated before proceeding. Reversal of such responses with flumazenil has been reported in pediatric and adult patients.

Concomitant Use of Central Nervous System Depressants

Concomitant use of barbiturates, alcohol or other central nervous system depressants may increase the risk of hypoventilation, airway obstruction, desaturation, or apnea and may contribute to profound and/or prolonged drug effect. Narcotic premedication also depresses the ventilatory response to carbon dioxide stimulation.

Drug-Drug Interactions

Coadministration of oral midazolam in patients who are taking ketoconazole and intraconazole, and saquinavir has been shown to result in large increases in Cmax and AUC of midazolam due to a decrease in plasma clearance of midazolam [see CLINICAL PHARMACOLOGY: Pharmacokinetics: Special Populations: Drug-Drug Interactions and PRECAUTIONS]. Due to the potential for intense and prolonged sedation and respiratory depression, midazolam HCI syrup should only be coadministered with these medications if absolutely necessary and with appropriate equipment and personnel available to respond to respiratory insufficiency.

Debilitation and Comorbidity Considerations

Higher risk pediatric surgical patients may require lower doses, whether or not concomitant sedating medications have been administered. Pediatric patients with cardiac or respiratory compromise may be unusually sensitive to the respiratory depressant effect of midazolam. Pediatric patients undergoing procedures involving the upper airway such as upper endoscopy or dental care, are particularly vulnerable to episodes of desaturation and hypoventilation due to partial airway obstruction. Patients with chronic renal failure and patients with congestive heart failure eliminate midazolam more slowly [see CLINICAL PHARMACOLOGY].

Return to Cognitive Function

Midazolam is associated with a high incidence of partial or complete impairment of recall for the next several hours. The decision as to when patients who have received midazolam HCl syrup, particularly on an outpatient basis, may again engage in activities requiring complete mental alertness, operate hazardous machinery or drive a motor vehicle must be individualized. Gross tests of recovery from the effects of midazolam HCl syrup [see CLINICAL PHARMACOLOGY] cannot be relied upon to predict reaction time under stress. It is recommended that no patient operate hazardous machinery or a motor vehicle until the effects of the drug, such as drowsiness, have subsided or until one full day after anesthesia and surgery, whichever is longer. Particular care should be taken to assure safe ambulation.

Neonatal Sedation and Withdrawal Syndrome

Use of midazolam HCl syrup late in pregnancy can result in sedation (respiratory depression, lethargy, hypotonia) and/or withdrawal symptoms (hyperreflexia, irritability, restlessness, tremors, inconsolable crying, and feeding difficulties) in the neonate [see PRECAUTIONS: Pregnancy]. Monitor neonates exposed to midazolam HCl syrup during pregnancy or labor for signs of sedation and monitor neonates exposed to midazolam HCl syrup during pregnancy for signs of withdrawal; manage these neonates accordingly.

Usage in Preterm Infants and Neonates

Midazolam HCl syrup has not been studied in patients less than 6 months of age.

Pediatric Neurotoxicity

Published animal studies demonstrate that the administration of anesthetic and sedation drugs that block NMDA receptors and/or potentiate GABA activity increase neuronal apoptosis in the developing brain and result in long-term cognitive deficits when used for longer than 3 hours. The clinical significance of these findings in not clear. However, based on the available date, the window of vulnerability to these changes is believed to correlate with exposures in the third trimester of gestation through the first several months of life, but may extend out to approximately three years of age in humans [see PRECAUTIONS; Pregnancy, Pediatric Use and ANIMAL PHARMACOLOGY AND/OR TOXICOLOGY].

Some published studies in children suggest that similar deficits may occur after repeated or prolonged exposures to anesthetic agents early in life and may result in adverse cognitive or behavioral effects. These studies have substantial limitations, and it is not clear if the observed effects are due to the anesthetic/sedation drug administration or other factors such as the surgery or underlying illness.

Anesthetic and sedation drugs are a necessary part of the care of children and pregnant women needing surgery, other procedures, or tests that cannot be delayed, and no specific medications have been shown to be safer than any other. Decisions regarding the timing of any elective procedures requiring anesthesia should take into consideration the benefits of the procedure weighed against the potential risks.

PRECAUTIONS

General

The efficacy and safety of midazolam in clinical use are functions of the dose administered, the clinical status of the individual patient, and the use of concomitant medications capable of depressing the CNS. Anticipated effects may range from mild sedation to deep levels of sedation with a potential loss of protective reflexes, particularly when coadministered with anesthetic agents or other CNS depressants. Care must be taken to individualize the dose of midazolam HCl syrup based on the patient's age, underlying medical/surgical conditions, concomitant medications, and to have the personnel, age- and size-appropriate equipment and facilities available for monitoring and intervention. Practitioners administering midazolam must have the skills necessary to manage reasonably foreseeable adverse effects, particularly skills in airway management.

Information for Patients

To assure safe and effective use of midazolam HCl syrup, the following information and instructions should be communicated to the patient when appropriate:

1. Inform your physician about any alcohol consumption and medicine you are now taking, especially blood pressure medication, antibiotics, and protease inhibitors, including drugs you buy without a prescription. Alcohol has an increased effect when consumed with benzodiazepines; therefore, caution should be exercised regarding simultaneous ingestion of alcohol during benzodiazepine treatment.
2. Inform your physician if you are pregnant or are planning to become pregnant.
3. Inform your physician if you are nursing.
4. Patients should be informed of the pharmacological effects of midazolam HCl syrup, such as sedation and amnesia, which in some patients may be profound. The decision as to when patients who have received midazolam HCl syrup, particularly on an outpatient basis, may again engage in activities requiring complete mental alertness, operate hazardous machinery or drive a motor vehicle must be individualized.
5. Midazolam should not be taken in conjunction with grapefruit juice.
6. For pediatric patients, particular care should be taken to assure safe ambulation.
7. Effect of Anesthetic and Sedation Drugs on Early Brain Development: Studies conducted in young animals and children suggest repeated or prolonged use of general anesthetic or sedation drugs in children younger than 3 years may have negative effects on their developing brains. Discuss with parents and caregivers the benefits, risks, and timing and duration of surgery or procedures requiring anesthetic and sedation drugs.

Pregnancy

Advise pregnant females that use of midazolam HCl syrup late in pregnancy can result in sedation (respiratory depression, lethargy, hypotonia) and/or withdrawal symptoms (hyperreflexia, irritability, restlessness, tremors, inconsolable crying, and feeding difficulties) in newborns [see WARNINGS: Neonatal Sedation and Withdrawal Syndrome and PRECAUTIONS: Pregnancy].

Instruct patients to inform their healthcare provider if they are pregnant.

Advise patients that there is a pregnancy exposure registry that monitors pregnancy outcomes in women exposed to midazolam HCl syrup during pregnancy [see PRECAUTIONS, Pregnancy].

Nursing

Instruct patients to notify their healthcare provider if they are breastfeeding or intend to breastfeed. Instruct breastfeeding patients receiving midazolam to monitor infants for excessive sedation, poor feeding, and poor weight gain, and to seek medical attention if they notice these signs. A lactating woman may consider pumping and discarding breastmilk for at least 4 to 8 hours after receiving midazolam for sedation or anesthesia to minimize drug exposure to a breastfed infant [see PRECAUTIONS, Nursing Mothers].

Drug Interactions

Effect of Concomitant Use of Benzodiazepines and Opioids

The concomitant use of benzodiazepines and opioids increases the risk of respiratory depression because of actions at different receptor sites in the CNS that control respiration. Benzodiazepines interact at GABAA sites, and opioids interact primarily at mu receptors. When benzodiazepines and opioids are combined, the potential for benzodiazepines to significantly worsen opioid-related respiratory depression exists. Monitor patients closely for respiratory depression and sedation.

Other CNS Depressants

One case was reported of inadequate sedation with chloral hydrate and later with oral midazolam due to a possible interaction with methylphenidate administered chronically in a 2-year-old boy with a history of Williams syndrome. The difficulty in achieving adequate sedation may have been the result of decreased absorption of the sedatives due to both the gastrointestinal effects and stimulant effects of methylphenidate.

The sedative effect of midazolam HCl syrup is accentuated by any concomitantly administered medication which depresses the central nervous system, particularly opioids (e.g., morphine, meperidine, and fentanyl), propofol, ketamine, nitrous oxide, secobarbital and droperidol. Consequently, the dose of midazolam HCl syrup should be adjusted according to the type and amount of concomitant medications administered and the desired clinical response [see DOSAGE AND ADMINISTRATION].

No significant adverse interactions with common premedications (such as atropine, scopolamine, glycopyrrolate, diazepam, hydroxyzine, and other muscle relaxants) or local anesthetics have been observed.

Inhibitors of CYP3A4 Isozymes

Caution is advised when midazolam is administered concomitantly with drugs that are known to inhibit the cytochrome P450 3A4 enzyme system (ie, some drugs in the drug classes of azole antimycotics, protease inhibitors, calcium channel antagonists, and macrolide antibiotics). Drugs such as diltiazem, erythromycin, fluconazole, itraconazole, ketoconazole, saquinavir, and verapamil were shown to significantly increase the Cmax and AUC of orally administered midazolam. These drug interactions may result in increased and prolonged sedation due to a decrease in plasma clearance of midazolam. Although not studied, the potent cytochrome P450 3A4 inhibitors ritonavir and nelfinavir may cause intense and prolonged sedation and respiratory depression due to a decrease in plasma clearance of midazolam. Caution is advised when midazolam HCl syrup is used concomitantly with these drugs. Dose adjustments should be considered and possible prolongation and intensity of effect should be anticipated [see CLINICAL PHARMACOLOGY: Pharmacokinetics: Special Populations: Drug-Drug Interactions].

Inducers of CYP3A4 Isozymes

Cytochrome P450 inducers, such as rifampin, carbamazepine, and phenytoin, induce metabolism and cause a markedly decreased Cmax and AUC of oral midazolam in adult studies. Although clinical studies have not been performed, phenobarbital is expected to have the same effect. Caution is advised when administering midazolam to patients receiving these medications and if necessary dose adjustments should be considered.

Drug/Laboratory Test Interactions

Midazolam has not been shown to interfere with results obtained in clinical laboratory tests.

Carcinogenesis, Mutagenesis, Impairment of Fertility

Carcinogenesis

Midazolam maleate was administered with diet in mice and rats for 2 years at dosages of 1, 9, and 80 mg/ kg/day. In female mice in the highest dose (10 times the highest oral dose of 1.0 mg/kg for a pediatric patient, on a mg/m^2 basis) group there was a marked increase in the incidence of hepatic tumors. In high-dose (19 times the pediatric dose) male rats there was a small but statistically significant increase in benign thyroid follicular cell tumors. Dosages of 9 mg/kg/day of midazolam maleate (1 to 2 times the pediatric dose) did not increase the incidence of tumors in mice or rats. The pathogenesis of induction of these tumors is not known. These tumors were found after chronic administration, whereas human use will ordinarily be single or intermittent doses.

Mutagenesis

Midazolam HCl syrup did not have mutagenic activity in Salmonella typhimurium (5 bacterial strains), Chinese hamster lung cells (V79), human lymphocytes or in the micronucleus test in mice.

Impairment of Fertility

Male rats were treated orally with 1, 4, or 16 mg/kg midazolam (0.2, 0.6, and 2.6 times the dose of 1 mg/kg based on body surface area) beginning 62 days prior to mating with female rats treated with the same doses for 14 days prior to mating to Gestation Day 13 or Lactation Day 21. There were no adverse effects on either male or female fertility noted.

Pregnancy

Pregnancy Exposure Registry

There is a pregnancy registry that monitors pregnancy outcomes in women exposed to psychiatric medications, including midazolam HCl syrup, during pregnancy. Healthcare providers are encouraged to register patients by calling the National Pregnancy Registry for Psychiatric Medications at 1-866-961-2388 or visiting online at https:// womensmentalhealth.org/pregnancyregistry/.

Risk Summary

Neonates born to mothers using benzodiazepines late in pregnancy have been reported to experience symptoms of sedation and/or neonatal withdrawal [see WARNINGS: Neonatal Sedation and Withdrawal Syndrome and Clinical Considerations]. Available data from published observational studies of pregnant women exposed to benzodiazepines do not report a clear association with benzodiazepines and major birth defects (see Data).

The background risk of major birth defects and miscarriage for the indicated population is unknown. All pregnancies have a background risk of birth defect, loss, or other adverse outcomes. In the U.S. general population, the estimated risk of major birth defects and of miscarriage in clinically recognized pregnancies is 2 to 4% and 15 to 20%, respectively.

Clinical Considerations

Fetal/Neonatal Adverse Reactions

Benzodiazepines cross the placenta and may produce respiratory depression, hypotonia and sedation in neonates. Monitor neonates exposed to midazolam HCl syrup during pregnancy and labor for signs of sedation, respiratory depression, hypotonia, and feeding problems. Monitor neonates exposed to midazolam HCl syrup during pregnancy for signs of withdrawal. Manage these neonates accordingly [see WARNINGS: Neonatal Sedation and Withdrawal Syndrome].

Data

Human Data

Published data from observational studies on the use of benzodiazepines during pregnancy do not report a clear association with benzodiazepines and major birth defects. Although early studies reported an increased risk of congenital malformations with diazepam and chlordiazepoxide, there was no consistent pattern noted. In addition, the majority of more recent case-control and cohort studies of benzodiazepine use during pregnancy, which were adjusted for confounding exposures to alcohol, tobacco and other medications, have not confirmed these findings.

Animal Data

Pregnant rats were treated with midazolam using intravenous doses of 0.2, 1, and 4 mg/kg/day (0.09, 0.46, and 1.85 times the human induction dose of 0.35 mg/kg based on body surface area comparisons) during the period of organogenesis (Gestation Day 7 through 15). Midazolam did not cause adverse effects to the fetus at doses of up to 1.85 times the human induction dose. All doses produced slight to moderate ataxia. The high dose produced a 5% decrease in maternal body weight gain compared to control.

Pregnant rabbits were treated with midazolam using intravenous doses of 0.2, 0.6, and 2 mg/kg/day (0.09, 0.46, and 1.85 times the human induction dose of 0.35 mg/kg based on body surface area comparisons) during the period of organogenesis (Gestation Day 7 to 18). Midazolam did not cause adverse effects to the fetus at doses of up to 1.85 times the human induction dose. The high dose was associated with findings of ataxia and sedation but no evidence of maternal toxicity.

Pregnant rats were administered midazolam using intravenous doses of 0.2, 1, and 4 mg/kg/day (0.09, 0.46, and 1.85 times the human induction dose of 0.35 mg/kg based on body surface area comparisons) during late gestation and through lactation (Gestation Day 15 through Lactation Day 21). All doses produced ataxia. The high dose produced a slight decrease in maternal body weight gain compared to control. There were no clear adverse effects noted in the offspring. The study included no functional assessments of the pups, such as learning and memory testing or reproductive capacity.

In a published study in primates, administration of an anesthetic dose of ketamine for 24 hours on Gestation Day 122 increased neuronal apoptosis in the developing brain of the fetus. In other published studies, administration of either isoflurane or propofol for 5 hours on Gestation Day 120 resulted in increased neuronal and oligodendrocyte apoptosis in the developing brain of the offspring. With respect to brain development, this time period corresponds to the third trimester of gestation in the human. The clinical significance of these findings is not clear; however, studies in juvenile animals suggest neuroapoptosis correlates with long-term cognitive deficits [see WARNINGS; Pediatric Neurotoxicity, PRECAUTIONS; Pediatric Use, and ANIMAL PHARMACOLOGY AND/OR TOXICOLOGY].

Nursing Mothers

Risk Summary

There are reports of sedation, poor feeding, and poor weight gain in infants exposed to benzodiazepines through breast milk. The developmental and health benefits of breastfeeding should be considered along with the mother's clinical need for Midazolam HCl syrup and any potential adverse effects on the breastfed infants from Midazolam HCl syrup or from the underlying maternal condition.

Clinical Considerations

Infants exposed to Midazolam HCl syrup through breast milk should be monitored for sedation, poor feeding and poor weight gain. A lactating woman may consider interrupting breastfeeding and pumping and discarding breast milk during treatment for a range of at least 4 to 8 hours after midazolam administration in order to minimize drug exposure to a breastfed infant.

Pediatric Use

Published juvenile animal studies demonstrate that the administration of anesthetic and sedation drugs, such as Midazolam Hydrochloride Syrup 2 mg/mL, that either block NMDA receptors or potentiate the activity of GABA during the period of rapid brain growth or synaptogenesis, results in widespread neuronal and oligodendrocyte cell loss in the developing brain and alterations in synaptic morphology and neurogenesis. Based on comparisons across species, the window of vulnerability to these changes is believed to correlate with exposures in the third trimester of gestation through the first several months of life, but may extend out to approximately 3 years of age in humans.

In primates, exposure to 3 hours of ketamine that produced a light surgical plane of anesthesia did not increase neuronal cell loss, however, treatment regimens of 5 hours or longer of isoflurane increased neuronal cell loss. Data from isoflurane-treated rodents and ketamine-treated primates suggest that the neuronal and oligodendrocyte cell losses are associated with prolonged cognitive deficits in learning and memory. The clinical significance of these nonclinical findings is not known, and healthcare providers should balance the benefits of appropriate anesthesia in pregnant women, neonates, and young children who require procedures with the potential risks suggested by the nonclinical data. [see WARNINGS; Pediatric Neurotoxicity, PRECAUTIONS; Pregnancy, and Pediatric Use and ANIMAL PHARMACOLOGY AND/OR TOXICOLOGY].

Geriatric Use

The safety and efficacy of this product have not been fully studied in geriatric patients. Therefore, there are no available data on a safe dosing regimen. One study in geriatric subjects, using midazolam 7.5 mg as a premedicant prior to general anesthesia, noted a 60% incidence of hypoxemia (pO2<90% for over 30 seconds) at sometime during the operative procedure versus 15% for the nonpremedicated group. Until further information is available it is recommended that this product should not be used in geriatric patients.

Use in Patients With Heart Disease

Following oral administration of 7.5 mg of midazolam to adult patients with congestive heart failure, the half-life of midazolam was 43% higher than in control subjects. One study suggests that hypercarbia or hypoxia following premedication with oral midazolam might pose a risk to children with congenital heart disease and pulmonary hypertension, although there are no known reports of pulmonary hypertensive crisis that had been triggered by premedication. In the study, 22 children were premedicated with oral midazolam (0.75 mg/kg) or IM morphine plus scopolamine prior to elective repair of congenital cardiac defects. Both premedication regimens increased PtcCO2 and decreased SpO2 and respiratory rates preferentially in patients with pulmonary hypertension.

ADVERSE REACTIONS

The distribution of adverse events occurring in patients evaluated in a randomized, double-blind, parallel-group trial are presented in Tables 5 and 6 by body system in order of decreasing frequency: for the premedication period (eg, sedation period prior to induction of anesthesia) alone, see Table 5; for over the entire monitoring period including premedication, anesthesia and recovery, see Table 6.

The distribution of adverse events occurring during the premedication period, before induction of anesthesia, is presented in Table 5. Emesis, which occurred in 31/397 (8%) patients over the entire monitoring period, occurred in 3/397 (0.8%) of patients during the premedication period (from midazolam administration to mask induction). Nausea, which occurred in 14/397 (4%) patients over the entire monitoring period (premedication, anesthesia and recovery), occurred in 2/397 (0.5%) patients during the premedication period.

This distribution of all adverse events occurring in ≥1% of patients over the entire monitoring period are presented in Table 6. For the entire monitoring period (premedication, anesthesia and recovery), adverse events were reported by 82/397 (21%) patients who received midazolam overall. The most frequently reported adverse events were emesis occurring in 31/397 (8%) patients and nausea occurring in 14/397 (4%) patients. Most of these gastrointestinal events occurred after the administration of other anesthetic agents.

For the respiratory system overall, adverse events (hypoxia, laryngospasm, rhonchi, coughing, respiratory depression, airway obstruction, upper-airway congestion, shallow respirations), occurred during the entire monitoring period in 31/397 (8%) patients and increased in frequency as dosage was increased: 7/132 (5%) patients in the 0.25 mg/kg dose group, 9/132 (7%) patients in the 0.5 mg/kg dose group, and 15/133 (11%) patients in the 1.0 mg/kg dose group.

Most of the respiratory adverse events occurred during induction, general anesthesia or recovery. One patient (0.25%) experienced a respiratory system adverse event (laryngospasm) during the premedication period. This adverse event occurred precisely at the time of induction. Although many of the respiratory complications occurred in settings of upper airway procedures or concurrently administered opioids, a number of these events occurred outside of these settings as well. In this study, administration of midazolam HCl syrup was generally accompanied by a slight decrease in both systolic and diastolic blood pressures, as well as a slight increase in heart rate.

Table 5: Adverse Events Occurring During the Premedication Period Before Mask Induction in the Randomized, Double-Blind, Parallel-Group Trial
Body System | Treatment Regimen |  |  |  |  |  | Overall
No. Patients with Adverse Events | 0.25 mg/kg (n=132) |  | 0.50 mg/kg (n=132) |  | 1.0 mg/kg (n=133) |  | (n=397)
 | No. | % | No. | % | No. | % | No. | %
Gastrointestinal System Disorders
Emesis | 1 | (0.76%) | 1 | (0.76%) | 1 | (0.75%) | 3 | (0.76%)
Nausea |  |  |  |  | 2 | (1.5%) | 2 | (0.50%)
Respiratory System Disorders
Laryngospasm |  |  |  |  | 1 [This adverse event occurred precisely at the time of induction.] | (0.75%) | 1 | (0.25%)
Sneezing/ Rhinorrhea |  |  |  |  | 1 | (0.75%) | 1 | (0.25%)
ALL BODY SYSTEMS | 1 | (0.76%) | 1 | (0.76%) | 5 | (3.8%) | 7 | (1.8%)

Table 6: Adverse Events (≥1%) From the Randomized, Double-Blind, Parallel-Group Trial on Entire Monitoring Period (premedication, anesthesia, recovery)
Body System | Treatment Regimen |  |  |  |  |  | Overall
No. Patients with Adverse Events | 0.25 mg/kg (n=132) |  | 0.50 mg/kg (n=132) |  | 1.0 mg/kg (n=133) |  | (n=397)
 | No. | % | No. | % | No. | % | No. | %
Gastrointestinal System Disorders
Emesis | 11 | (8%) | 5 | (4%) | 15 | (11%) | 31 | (8%)
Nausea | 6 | (5%) | 2 | (2%) | 6 | (5%) | 14 | (4%)
Overall | 16 | (12%) | 8 | (6%) | 16 | (12%) | 40 | (10%)
Respiratory System Disorders
Hypoxia | 0 |  | 5 | (4%) | 4 | (3%) | 9 | (2%)
Laryngospasm | 0 |  | 1 | (<1%) | 5 | (4%) | 6 | (2%)
Respiratory Depression | 2 | (2%) | 1 | (<1%) | 2 | (2%) | 5 | (1%)
Rhonchi | 2 | (2%) | 1 | (<1%) | 2 | (2%) | 5 | (1%)
Airway Obstruction | 2 | (2%) | 2 | (2%) | 0 |  | 4 | (1%)
Upper Airway Congestion | 2 | (2%) | 0 |  | 2 | (2%) | 4 | (1%)
Overall | 7 | (5%) | 9 | (7%) | 15 | (11%) | 31 | (8%)
Psychiatric Disorders
Agitated | 1 | (<1%) | 2 | (2%) | 3 | (2%) | 6 | (2%)
Overall | 1 | (<1%) | 3 | (2%) | 4 | (11%) | 8 | (2%)
Heart Rate, Rhythm Disorders
Bradycardia | 1 | (<1%) | 3 | (2%) | 0 |  | 4 | (1%)
Bigeminy | 2 | (2%) | 0 |  | 0 |  | 2 | (<1%)
Overall | 3 | (2%) | 3 | (2%) | 1 | (<1%) | 7 | (2%)
Central & Peripheral Nervous System Disorders
Prolonged Sedation | 0 |  | 0 |  | 2 | (2%) | 2 | (<1%)
Overall | 2 | (2%) | 0 |  | 3 | (2%) | 5 | (1%)
Skin and Appendages Disorders
Rash | 2 | (2%) | 0 |  | 0 |  | 2 | (<1%)
Overall | 2 | (2%) | 2 | (2%) | 0 |  | 4 | (1%)
ALL BODY SYSTEMS | 26 | (20%) | 23 | (17%) | 33 | (25%) | 82 | (21%)

There were no deaths during the study and no patient withdrew from the study due to adverse events. Serious adverse events (both respiratory disorders) were experienced postoperatively by two patients: one case of airway obstruction and desaturation (SpO2 of 33%) in a patient given midazolam HCl syrup 0.25 mg/kg, and one case of upper airway obstruction and respiratory depression following 0.5 mg/kg. Both patients had received intravenous morphine sulfate (1.5 mg total for both patients).

Other adverse events that have been reported in the literature with the oral administration of midazolam (not necessarily midazolam HCl syrup), are listed below. The incidence rate for these events was generally <1%.

Respiratory: apnea, hypercarbia, desaturation, stridor.

Cardiovascular: decreased systolic and diastolic blood pressure, increased heart rate.

Gastrointestinal: nausea, vomiting, hiccoughs, gagging, salivation, drooling.

Central Nervous System: dysphoria, disinhibition, excitation, aggression, mood swings, hallucinations, adverse behavior, agitation, dizziness, confusion, ataxia, vertigo, dysarthria.

Special Senses: diplopia, strabismus, loss of balance, blurred vision.

DRUG ABUSE AND DEPENDENCE

Midazolam HCl syrup is a benzodiazepine and is a Schedule IV controlled substance that can produce drug dependence of the diazepam-type. Therefore, midazolam HCl syrup may be subject to misuse, abuse and addiction. Benzodiazepines can cause physical dependence. Physical dependence results in withdrawal symptoms in patients who abruptly discontinue the drug. Withdrawal symptoms (ie, convulsions, hallucinations, tremors, abdominal and muscle cramps, vomiting and sweating), similar in characteristics to those noted with barbiturates and alcohol have occurred following abrupt discontinuation of midazolam following chronic administration. Abdominal distention, nausea, vomiting, and tachycardia are prominent symptoms of withdrawal in infants.

The handling of midazolam HCl syrup should be managed to minimize the risk of diversion, including restriction of access and accounting procedures as appropriate to the clinical setting and as required by law.

OVERDOSAGE

Clinical Presentation

Overdosage of benzodiazepines is characterized by central nervous system depression ranging from drowsiness to coma. In mild to moderate cases, symptoms can include drowsiness, confusion, dysarthria, lethargy, hypnotic state, diminished reflexes, ataxia, and hypotonia. Rarely, paradoxical or disinhibitory reactions (including agitation, irritability, impulsivity, violent behavior, confusion, restlessness, excitement, and talkativeness) may occur. In severe overdosage cases, patients may develop respiratory depression and coma. Overdosage of benzodiazepines in combination with other CNS depressants (including alcohol and opioids) may be fatal [see WARNINGS: Dependence and Withdrawal Reactions]. Markedly abnormal (lowered or elevated) blood pressure, heart rate, or respiratory rate raise the concern that additional drugs and/or alcohol are involved in the overdosage.

Management of Overdose

In managing benzodiazepine overdosage, employ general supportive measures, including intravenous fluids and airway management. Flumazenil, a specific benzodiazepine receptor antagonist, is indicated for the complete or partial reversal of the sedative effects of benzodiazepines in the management of benzodiazepine overdosage, can lead to withdrawal and adverse reactions, including seizures, particularly in the context of mixed overdosage with drugs that increase seizure risk (e.g., tricyclic and tetracyclic antidepressants) and in patients with long term benzodiazepine use and physical dependency. The risk of withdrawal seizures with flumazenil use may be increased in patients with epilepsy. Flumazenil is contraindicated in patients who have received a benzodiazepine for control of a potentially life-threatening condition (e.g., status epilepticus). If the decision is made to use flumazenil, it should be used as an adjunct to, not as a substitute for, supportive management of benzodiazepine overdosage. See the flumazenil injection Prescribing Information.

Consider contacting a poison center (1-800-222-1222), poisoncontrol.org, or a medical toxicologist for additional overdosage management recommendations.

DOSAGE AND ADMINISTRATION

Midazolam HCl syrup is indicated for use as a single dose (0.25 to 1.0 mg/kg with a maximum dose of 20 mg) for preprocedural sedation and anxiolysis in pediatric patients. Midazolam HCl syrup is not intended for chronic administration.

Monitoring

Midazolam HCl syrup should only be used in hospital or ambulatory care settings, including physicians' and dentists' offices that can provide for continuous monitoring of respiratory and cardiac function. Immediate availability of resuscitative drugs and age- and size-appropriate equipment for bag/valve/mask ventilation and intubation, and personnel trained in their use and skilled in airway management should be assured [see WARNINGS]. For deeply sedated patients, a dedicated individual whose sole responsibility it is to observe the patient, other than the practitioner performing the procedure, should monitor the patient throughout the procedure. Continuous monitoring of respiratory and cardiac function is required.

Midazolam HCl syrup must be given only to patients if they will be monitored by direct visual observation by a health care professional. Midazolam HCl syrup should only be administered by persons specifically trained in the use of anesthetic drugs and the management of respiratory effects of anesthetic drugs, including respiratory and cardiac resuscitation of patients in the age group being treated.

Patient response to sedative agents, and resultant respiratory status, is variable. Regardless of the intended level of sedation or route of administration, sedation is a continuum; a patient may move easily from light to deep sedation, with potential loss of protective reflexes, particularly when coadministered with anesthetic agents, other CNS depressants, and concomitant medications which may potentially cause a more intense and prolonged sedation [see PRECAUTIONS: Drug Interactions]. This is especially true in pediatric patients. The health care practitioner who uses this medication in pediatric patients should be aware of and follow accepted professional guidelines for pediatric sedation appropriate to their situation.

Sedation guidelines recommend a careful presedation history to determine how a patient's underlying medical conditions or concomitant medications might affect their response to sedation/analgesia as well as a physical examination including a focused examination of the airway for abnormalities. Further recommendations include appropriate presedation fasting.

Intravenous access is not thought to be necessary for all pediatric patients sedated for a diagnostic or therapeutic procedure because in some cases the difficulty of gaining IV access would defeat the purpose of sedating the child; rather, emphasis should be placed upon having the intravenous equipment available and a practitioner skilled in establishing vascular access in pediatric patients immediately available.

Midazolam HCl syrup must never be used without individualization of dosage, particularly when used with other medications capable of producing CNS depression. Younger (<6 years of age) pediatric patients may require higher dosages (mg/kg) than older pediatric patients, and may require close monitoring.

When midazolam HCl syrup is given in conjunction with opioids or other sedatives, the potential for respiratory depression, airway obstruction, or hypoventilation is increased. For appropriate patient monitoring, see WARNINGS and DOSAGE AND ADMINISTRATION: Monitoring. The health care practitioner who uses this medication in pediatric patients should be aware of and follow accepted professional guidelines for pediatric sedation appropriate to their situation.

The recommended dose for pediatric patients is a single dose of 0.25 to 0.5 mg/kg, depending on the status of the patient and desired effect, up to a maximum dose of 20 mg. In general, it is recommended that the dose be individualized and modified based on patient age, level of anxiety, concomitant medications, and medical need [see WARNINGS and PRECAUTIONS]. The younger (6 months to <6 years of age) and less cooperative patients may require a higher than usual dose up to 1.0 mg/kg. A dose of 0.25 mg/kg may suffice for older (6 to <16 years of age) or cooperative patients, especially if the anticipated intensity and duration of sedation is less critical. For all pediatric patients, a dose of 0.25 mg/kg should be considered when midazolam HCl syrup is administered to patients with cardiac or respiratory compromise, other higher risk surgical patients, and patients who have received concomitant narcotics or other CNS depressants. As with any potential respiratory depressant, these patients must be monitored for signs of cardiorespiratory depression after receiving midazolam HCl syrup. In obese pediatric patients, the dose should be calculated based on ideal body weight. Midazolam HCl syrup has not been studied, nor is it intended for chronic use.

DISPOSAL OF MIDAZOLAM HCl SYRUP

The disposal of Schedule IV controlled substances must be consistent with State and Federal Regulations.

HOW SUPPLIED

Midazolam Hydrochloride Syrup

Midazolam HCl Syrup is supplied as a clear, red to purplish-red, cherry-brandy flavored syrup containing midazolam hydrochloride equivalent to 2 mg of midazolam/mL.

NDC 68094-762-62
2.5 mL per unit dose cup
Thirty (30) cups per shipper

NDC 68094-764-62
5 mL per unit dose cup
Thirty (30) cups per shipper

STORAGE AND HANDLING

Store at 20° to 25°C (68° to 77°F). [See USP Controlled Room Temperature.]

ANIMAL PHARMACOLOGY AND/OR TOXICOLOGY

Published studies in animals demonstrate that the use of anesthetic agents during the period of rapid brain growth or synaptogenesis results in widespread neuronal and oligodendrocyte cell loss in the developing brain and alterations in synaptic morphology and neurogenesis. Based on comparisons across species, the window of vulnerability to these changes is believed to correlate with exposures in the third trimester through the first several months of life, but may extend out to approximately 3 years of age in humans.

In primates, exposure to 3 hours of exposure to an anesthetic regimen that produced a light surgical plane of anesthesia did not increase neuronal cell loss, however, treatment regimens of 5 hours or longer increased neuronal cell loss. Data in rodents and in primates suggest that the neuronal and oligodendrocyte cell losses are associated with subtle but prolonged cognitive deficits in learning and memory. The clinical significance of these nonclinical findings is not known, and healthcare providers should balance the benefits of appropriate anesthesia in neonates and young children who require procedures against the potential risks suggested by the nonclinical data [see WARNINGS; Pediatric Neurotoxicity and PRECAUTIONS; Pregnancy and Pediatric Use].

Packaged by:
Precision Dose, Inc.
South Beloit, IL 61080

For inquiries call Precision Dose, Inc. at 1-800-397-9228 or email druginfo@precisiondose.com

LI1761 Rev. 11/24

PRINCIPAL DISPLAY PANEL - 5 mL Dose Cup Label

NDC 68094-764-59
PrecisionDose™

MIDAZOLAM
Hydrochloride Syrup
CIV
10 mg/5 mL

Pkg: Precision Dose, Inc., S. Beloit, IL 61080